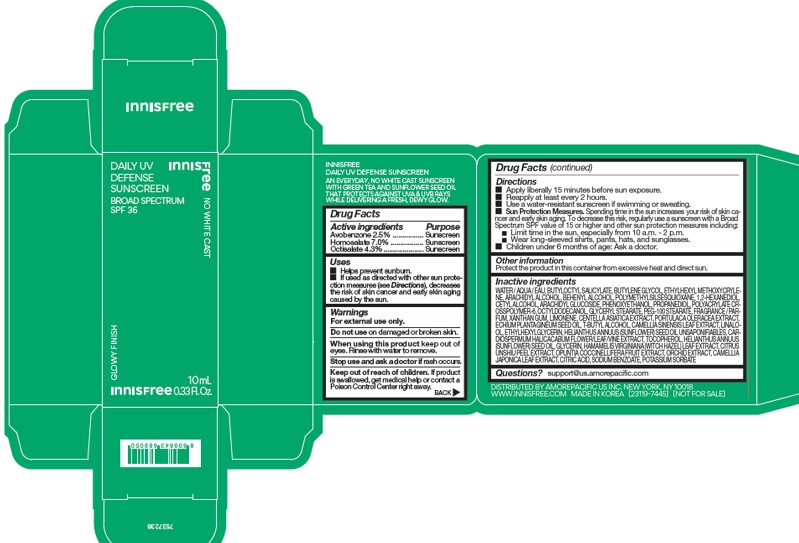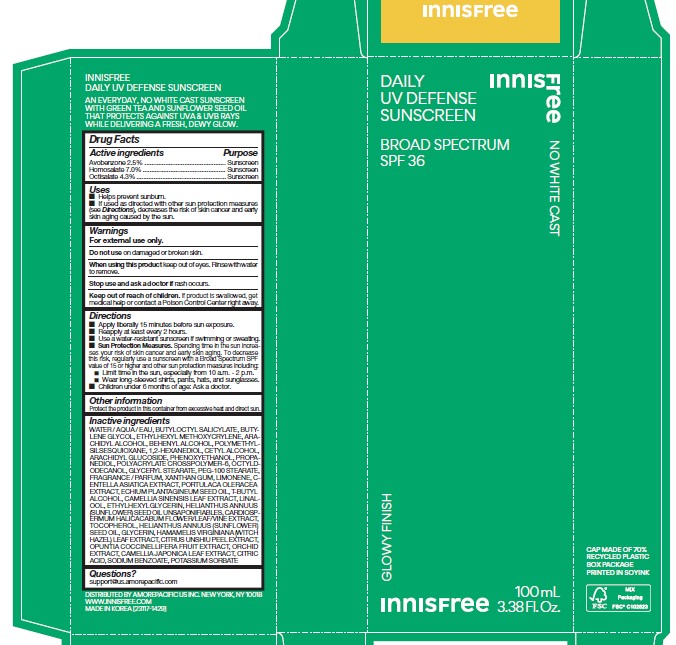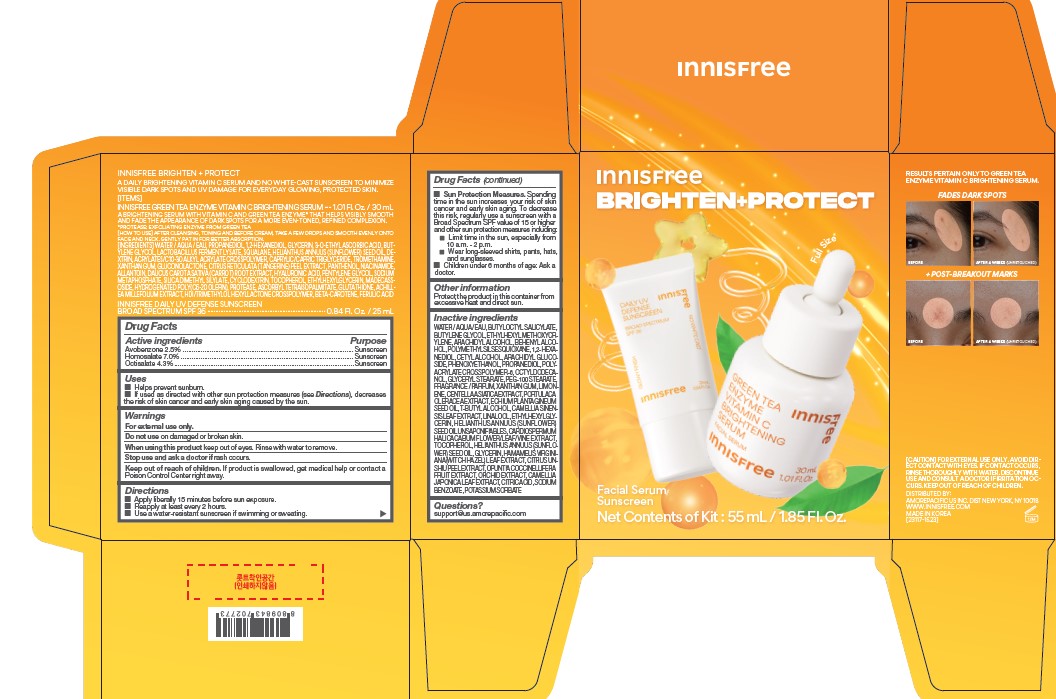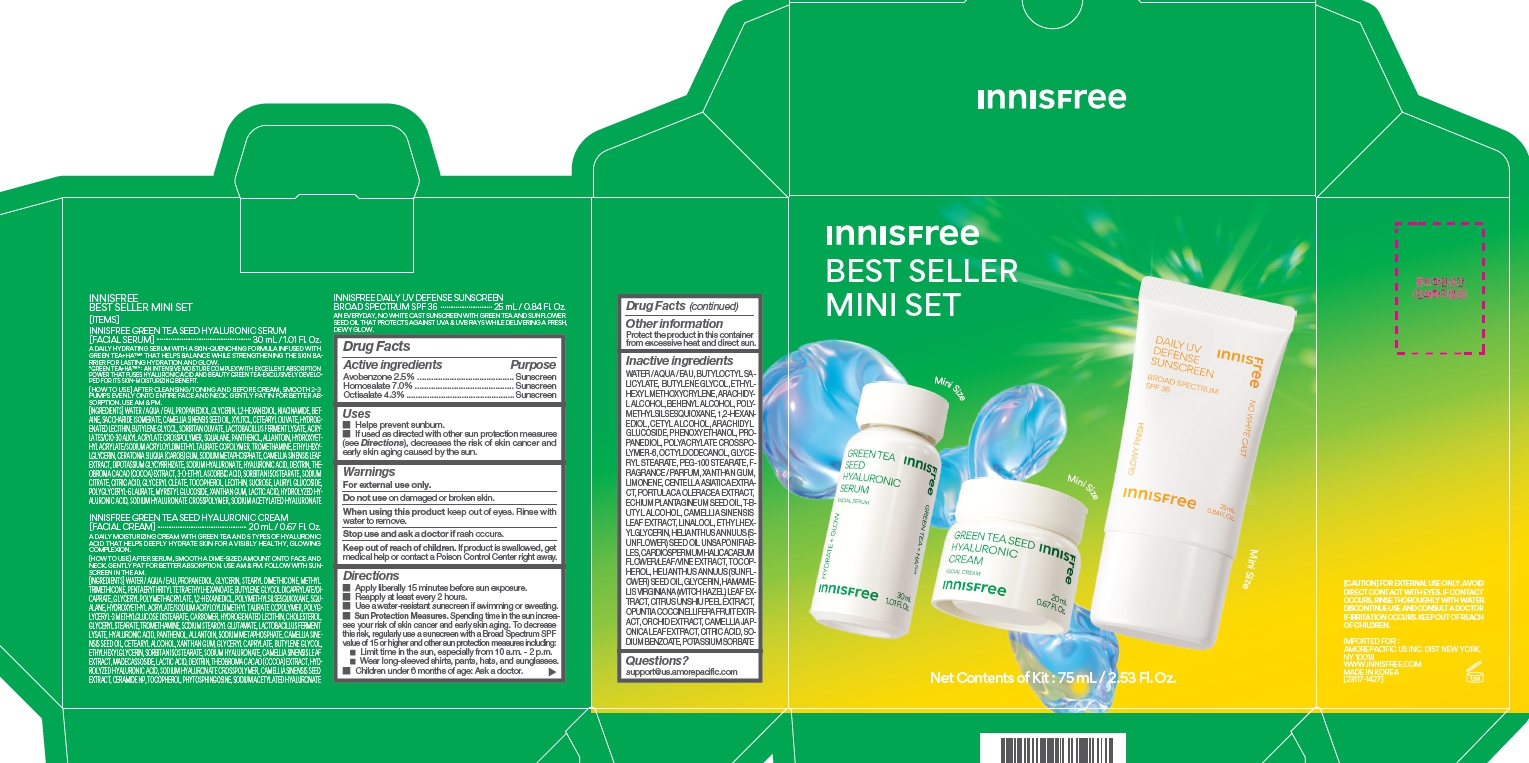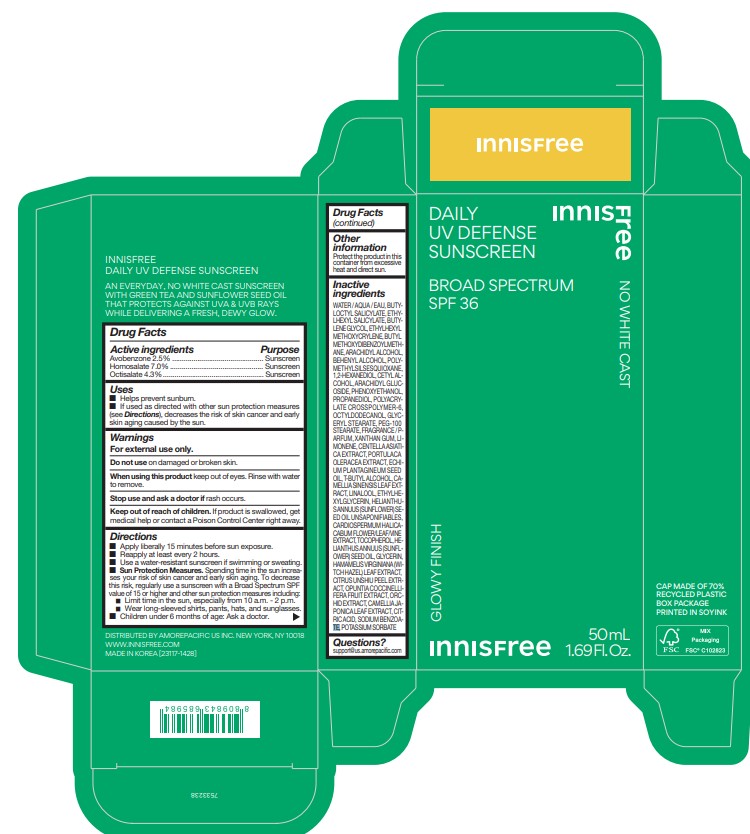 DRUG LABEL: innisfree Daily UV Defense Sunscreen
NDC: 71220-086 | Form: LOTION
Manufacturer: Innisfree Corporation
Category: otc | Type: HUMAN OTC DRUG LABEL
Date: 20251120

ACTIVE INGREDIENTS: AVOBENZONE 1.25 g/50 mL; HOMOSALATE 3.5 g/50 mL; OCTISALATE 2.15 g/50 mL
INACTIVE INGREDIENTS: OCTYLDODECANOL; ECHIUM PLANTAGINEUM SEED OIL; LINALOOL, (+/-)-; POTASSIUM SORBATE; TOCOPHEROL; GLYCERIN; CYCNOCHES COOPERI FLOWERING TOP; POLYMETHYLSILSESQUIOXANE (4.5 MICRONS); ETHYLHEXYL METHOXYCRYLENE; ARACHIDYL ALCOHOL; CETYL ALCOHOL; PROPANEDIOL; AMMONIUM ACRYLOYLDIMETHYLTAURATE, DIMETHYLACRYLAMIDE, LAURYL METHACRYLATE AND LAURETH-4 METHACRYLATE COPOLYMER, TRIMETHYLOLPROPANE TRIACRYLATE CROSSLINKED (45000 MPA.S); PEG-100 STEARATE; LIMONENE, (+)-; CENTELLA ASIATICA TRITERPENOIDS; GREEN TEA LEAF; ETHYLHEXYLGLYCERIN; SUNFLOWER OIL UNSAPONIFIABLES; SUNFLOWER OIL; CARDIOSPERMUM HALICACABUM FLOWERING TOP; TANGERINE PEEL; OPUNTIA COCHENILLIFERA FRUIT; ARACHIDYL GLUCOSIDE; CAMELLIA JAPONICA LEAF; CITRIC ACID MONOHYDRATE; SODIUM BENZOATE; GLYCERYL MONOSTEARATE; TERT-BUTYL ALCOHOL; HAMAMELIS VIRGINIANA LEAF; BUTYLENE GLYCOL; WATER; BUTYLOCTYL SALICYLATE; XANTHAN GUM; PURSLANE; DOCOSANOL; 1,2-HEXANEDIOL; PHENOXYETHANOL

innisfree Daily UV Defense Sunscreen BROAD SPECTRUM SPF 36

Drug Facts

ACTIVE INGREDIENTS

Avobenzone 2.5%

Homosalate 7.0%

Octisalate 4.3%

Purpose

Sunscreen

Uses

- Helps prevent sunburn
- If used as directed with other sun protection measures (see Directions), decreases the risk of skin cancer and early skin aging causes by the sun

Warnings

For external use only

Do not use on damanged or broken skin

When using this product keep out of eyes. Rinse with water to remove.

Stop use and ask a doctor if rash occurs.

Keep out of reach of children. If product is swallowed, get medical help or contact a Poison Control Center right away.

Directions

- Apply liberally 15 minutes before sun exposure.
- Reapply at least every 2 hours.
- Use a water-resistant sunscreen if swimming or sweating.
- Sun Protection Measures. Spending time in the sun increases your risk of skin cancer and early skin aging. To decrease this risk, regularly use a sunscreen with a Broad Spectrum SPF value of 15 or higher and other sun protection measures including :

- Limit time in the sun, especially from 10 a.m. - 2 p.m.

- Wear long-sleeved shirts, pants, hats, and sunglasses.

- Children under 6 months of age : Ask a doctor.

Inactive ingredients

WATER / AQUA / EAU, BUTYLOCTYL SALICYLATE, ETHYLHEXYL SALICYLATE, BUTYLENE GLYCOL, ETHYLHEXYL METHOXYCRYLENE, BUTYL METHOXYDIBENZOYLMETHANE, ARACHIDYL ALCOHOL, BEHENYL ALCOHOL, POLYMETHYLSILSESQUIOXANE, 1,2-HEXANEDIOL, CETYL ALCOHOL, ARACHIDYL GLUCOSIDE, PHENOXYETHANOL, PROPANEDIOL, POLYACRYLATE CROSSPOLYMER-6, OCTYLDODECANOL, GLYCERYL STEARATE, PEG-100 STEARATE, FRAGRANCE / PARFUM, XANTHAN GUM, LIMONENE, CENTELLA ASIATICA EXTRACT, PORTULACA OLERACEA EXTRACT, ECHIUM PLANTAGINEUM SEED OIL, T-BUTYL ALCOHOL, CAMELLIA SINENSIS LEAF EXTRACT, LINALOOL, ETHYLHEXYLGLYCERIN, HELIANTHUS ANNUUS (SUNFLOWER) SEED OIL UNSAPONIFIABLES, CARDIOSPERMUM HALICACABUM FLOWER/LEAF/VINE EXTRACT, TOCOPHEROL, HELIANTHUS ANNUUS (SUNFLOWER) SEED OIL, GLYCERIN, HAMAMELIS VIRGINIANA (WITCH HAZEL) LEAF EXTRACT, CITRUS UNSHIU PEEL EXTRACT, OPUNTIA COCCINELLIFERA FRUIT EXTRACT, ORCHID EXTRACT, CAMELLIA JAPONICA LEAF EXTRACT, CITRIC ACID, SODIUM BENZOATE, POTASSIUM SORBATE

Other information

Protect the product in this container from excessive heat and direct sun.

Questions?

support@us.amorepacific.com

Innisfree Daily UV Defense

Innisfree

DAILY UV

DEFENSE
SUNSCREEN
BROAD SPECTRUM
SPF 36

NO WHITE CAST

GLOWY FINISH

50 mL

1.69 Fl. Oz.

Innisfree Daily UV Defense 100mL

DAILY
UV DEFENSE
SUNSCREEN
BROAD SPECTRUM
SPF 36

NO WHITE CAST

GLOWY FINISH

100mL

3.38 Fl. Oz.

Innisfree Best Seller Mini set - Daily UV Defense 50 mL

Innisfree Best Seller Mini set

PACKAGE LABEL

Innisfree

DAILY UV

DEFENSE
SUNSCREEN
BROAD SPECTRUM
SPF 36

NO WHITE CAST

GLOWY FINISH

10 mL
0.33 Fl. Oz.

Innisfree Brighten+Protect set -- Daily UV Defense 25mL

Innisfree

Brighten+Protect